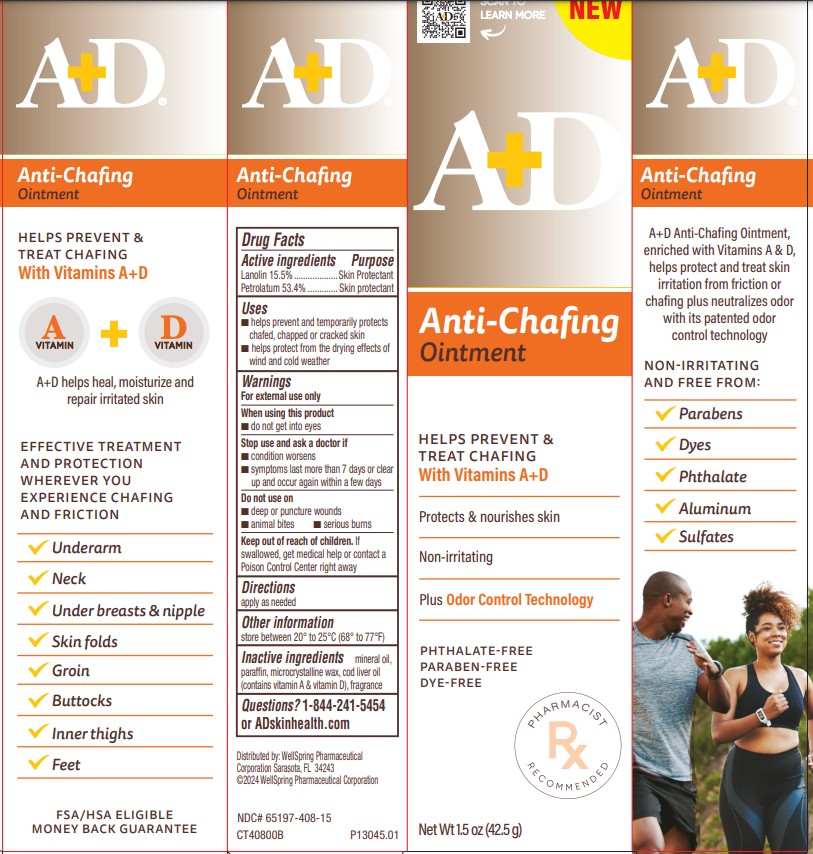 DRUG LABEL: AD Anti-Chafing
NDC: 65197-408 | Form: OINTMENT
Manufacturer: WellSpring Pharmaceutical Corporation
Category: otc | Type: HUMAN OTC DRUG LABEL
Date: 20250205

ACTIVE INGREDIENTS: LANOLIN 15.5 g/100 g; PETROLATUM 53.4 g/100 g
INACTIVE INGREDIENTS: MINERAL OIL; PARAFFIN; MICROCRYSTALLINE WAX; COD LIVER OIL

A+D Anti-Chafing Ointment 1.5 oz (42.5g)

Active Ingredients

Lanolin 15.5%

Petrolatum 53.4%

Purpose

Skin protectant

Skin protectant

Uses

- Helps prevent and temporarily protects chafed, chapped or cracked skin
- Helps protect from the drying effects of wind and cold weather

Warnings

For external use only

When using this product

- do not get into eyes

Stop use and ask a doctor if

- condition worsens
- symptoms last more than 7 days or clear up and occur again within a few days

Do not use on

- deep or puncture wounds
- animal bites
- serious burns

Keep out of reach of children

- If swallowed, get medical help or contact a Poison Control Center right away.

Directions

apply as needed

Other information

store between 20° to 25°C (68° to 77°F)

Inactive ingredients

mineral oil, paraffin, microcrystalline wax, cod liver oil (contains vitamin A & vitamin D), fragrance

Questions?

1-844-241-5454 or ADskinhealth.com

Distributed by:

WellSpring Pharmaceutical Corporation
Sarasota, FL 34243

© 2024 WellSpring Pharmaceutical Corporation

PACKAGE LABEL. PRINCIPAL DISPLAY PANEL

A+D Anti-Chafing Ointment 1.5 oz (42.5g)

HELPS PREVENT AND TREAT Chafing with Vitamins A+D

Protects & nourishes skin

Non-Irritating

Plus Odor Control Technology

NET WT 1.5 oz (42.5g)

CT40800B

NDC# 65197-408-15

P13045.01

CT40800B Anti-Chaffing Ointment